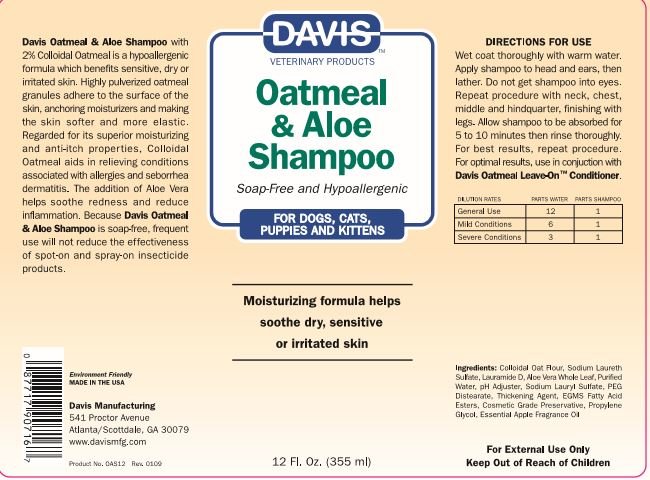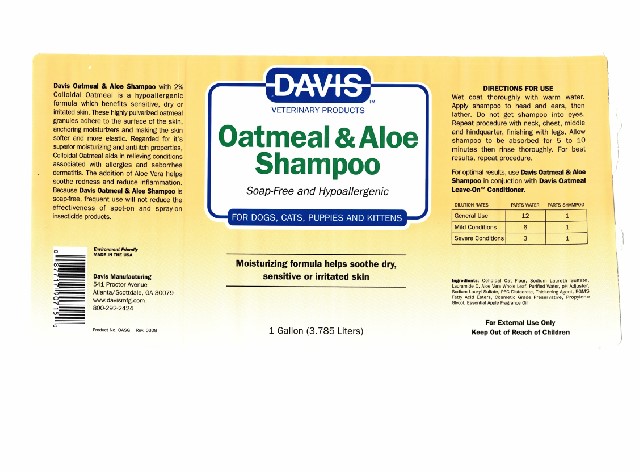 DRUG LABEL: Davis Oatmeal and Aloe
NDC: 62570-082 | Form: SHAMPOO
Manufacturer: Davis Manufacturing and Packaging Inc
Category: animal | Type: OTC ANIMAL DRUG LABEL
Date: 20191104

ACTIVE INGREDIENTS: OATMEAL 2 g/100 g
INACTIVE INGREDIENTS: ALOE VERA LEAF; SODIUM LAURETH SULFATE; SODIUM LAURYL SULFATE; COCAMIDOPROPYL BETAINE; COCO MONOETHANOLAMIDE; SODIUM CHLORIDE; PROPYLENE GLYCOL 1,2-DISTEARATE; C12-14 PARETH-12; STEARAMIDOPROPYL BETAINE; METHYLCHLOROISOTHIAZOLINONE/METHYLISOTHIAZOLINONE MIXTURE; PROPYLENE GLYCOL; ANHYDROUS CITRIC ACID

Davis Oatmeal & Aloe Shampoo

DESCRIPTION

Davis Oatmeal & Aloe Shampoo with 2% Colloidal Oatmeal is a hypoallergenic formula which benefits sensitive, dry or irritated skin. These highly pulverized oatmeal granules adhere to the surface of skin, anchoring moisturizers and making the skin softer and more elastic. Regarded for it’s superior moisturizing and anti-itch properties, Colloidal Oatmeal aids in the relieving conditions associated with allergies and seborrhea dermatitis. The addition of Aloe Vera helps soothe redness and reduce inflammation. Because Davis Oatmeal & Aloe Shampoo is soap-free, frequent use will not reduce the effectiveness of spot-on and spray-on insecticide products.

Environment Friendly

MADE IN THE USA

Davis Manufacturing

541 Proctor Avenue

Scottdale, GA 30079 (Atlanta)

800-292-2424

DOSAGE AND ADMINISTRATION

Dilution rates | Parts Water | Parts Shampoo
General Use | 12 | 1
Mild Conditions | 6 | 1
Severe Conditions | 3 | 1

DIRECTIONS FOR USE

Wet coat thoroughly with warm water. Apply shampoo to head and ears, then lather. Do not get into eyes. Repeat procedure with neck, chest, middle and hindquarter, finishing with legs. Allow shampoo to be absorbed for 5 to 10 minutes then rinse thoroughly. For best results, repeat procedure.

For optimal results, use Davis Oatmeal & Aloe Shampoo in conjunction with Davis Oatmeal Leave-OnTM Conditioner

INACTIVE INGREDIENT

Ingredients: Colloidal Oat Flour, Sodium Laureth Sulfate, Lauramide D, Aloe Whole Leaf, Purified Water, pH Adjuster, Sodium Lauryl Sulfate, PEG Distearate, Thickening Agent, EGMS, Fatty Acid Esters, Cosmetic Grade Preservative, Propylene Glycol, Essential Apple Fragrance Oil

WARNINGS AND PRECAUTIONS

FOR EXTERNAL USE ONLY

KEEP OUT OF REACH OF CHILDREN

Principal Display 355 ml

Davis Veterinary Products

Oatmeal & Aloe Shampoo

Soap-Free and Hypoallergenic

PACKAGE LABEL

Davis Veterinary Products

Oatmeal Leave-On TM Conditioner

Ultimate Mositurizing Formula

FOR DOGS, CATS, PUPPIES, AND KITTENS

Helps provide soothing residual relief for irritated, dry and itchy skin

1 Gallon (3.785 Liters)

Product No. OASG Rev. 0308